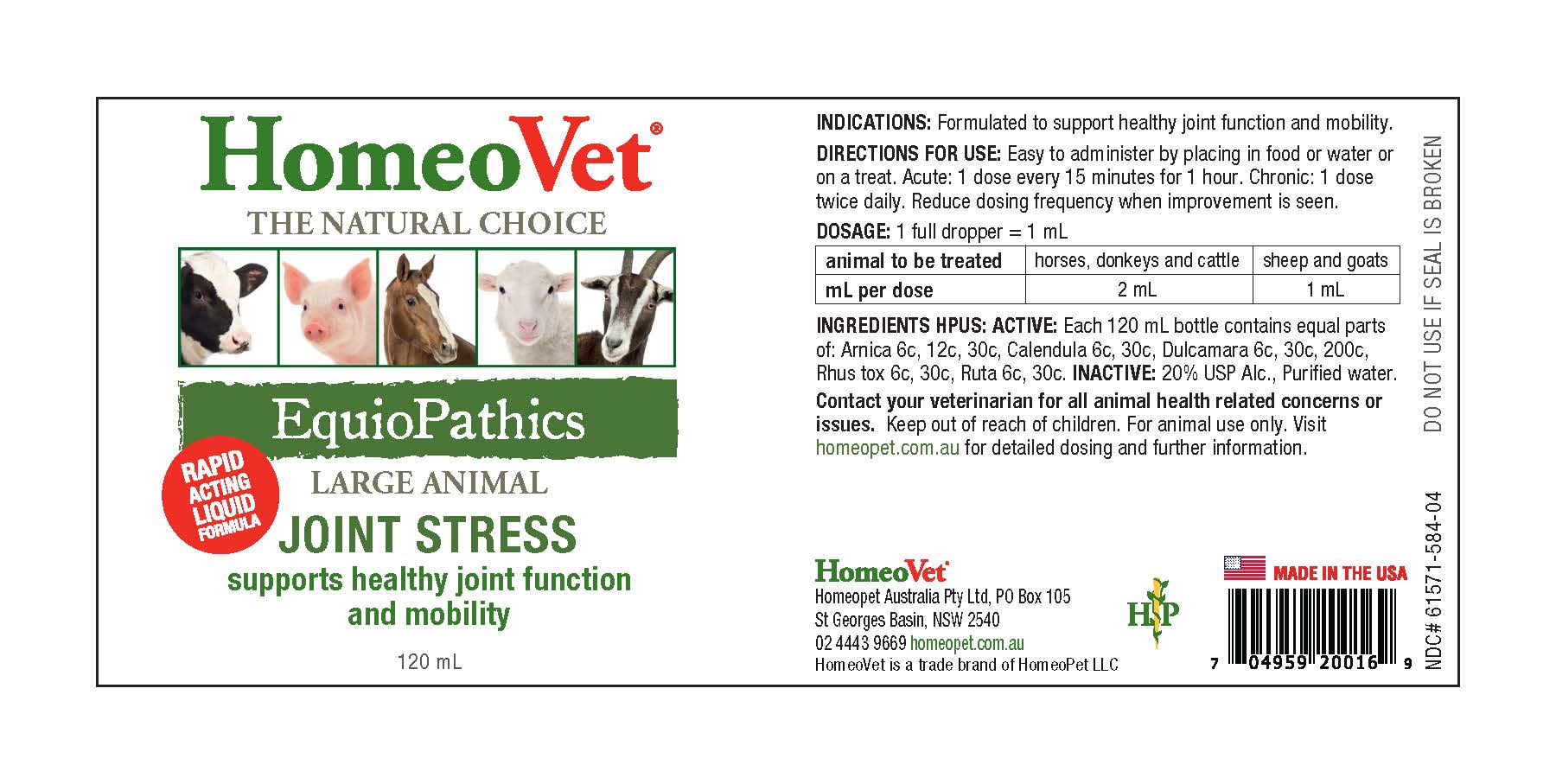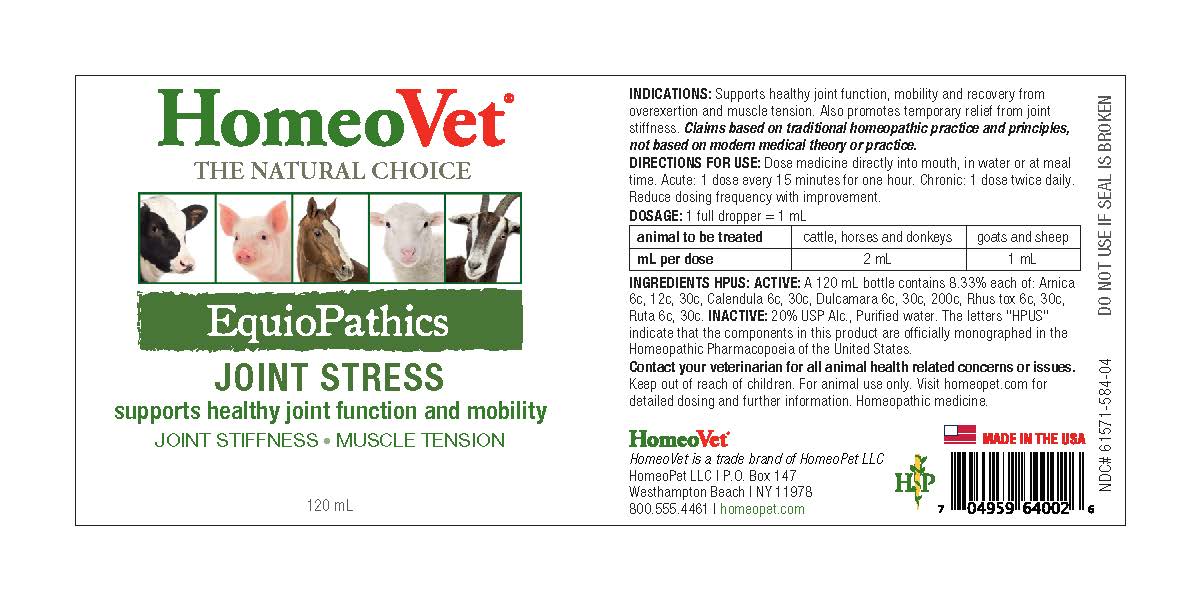 DRUG LABEL: Equiopathics Joint Stress
NDC: 61571-584 | Form: LIQUID
Manufacturer: HomeoPet, LLC
Category: homeopathic | Type: OTC ANIMAL DRUG LABEL
Date: 20251211

ACTIVE INGREDIENTS: TOXICODENDRON PUBESCENS LEAF 6 [hp_C]/120 mL; SOLANUM DULCAMARA FLOWER 6 [hp_C]/120 mL; RUTA GRAVEOLENS FLOWERING TOP 6 [hp_C]/120 mL; CALENDULA OFFICINALIS FLOWERING TOP 6 [hp_C]/120 mL; ARNICA MONTANA 6 [hp_C]/120 mL
INACTIVE INGREDIENTS: ALCOHOL; WATER

EquioPathics Joint Stress

DIRECTIONS FOR USE AND DOSAGE

Dose remedy directly into mouth, in water or at meal time. Acute: 1 dose every 15 minutes for one hour before travel. Chronic: 1 dose twice daily. Reduce dosing frequency with improvement.

animal to be treated | cattle, horses and donkeys | goats and sheep
mL per dose | 2 mL | 1 mL

Ingredients HPUS: Active

Arnica 6c, 12c, 30c, Calendula 6c, 30c, Dulcamara 6c, 30c, 200c, Rhus tox 6c, 30c, Ruta 6c, 30c

Inactive Ingredients

USP Alcohol, Purified Water

Contact Veterinary

Contact your veterinarian for all animal health related concerns or issues. Keep out of reach of children. For animal use only. Visit homeopet.com for detailed dosing and further information. Homeopathic medicine.

Precautions

Do not use if seal is broken.

INDICATIONS

Supports healthy joint function, mobility and recovery from overexertion and muscle tension. Also promotes temporary relief from joint stiffness. Claims based on traditional homeopathic practice and principles, not based on modern medical theory or practice.

EquioPathics Joint Stress

supports healthy joint function and mobility

JOINT STIFFNESS-MUSCLE TENSION